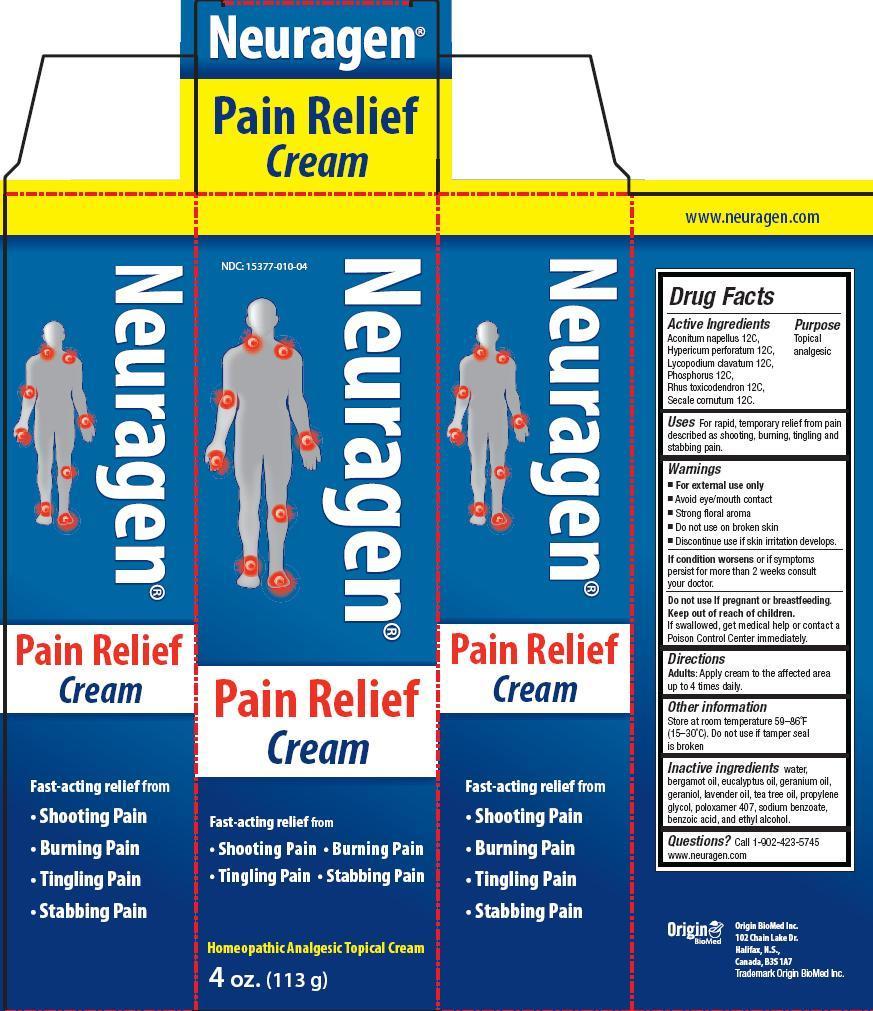 DRUG LABEL: Neuragen
NDC: 15377-010 | Form: CREAM
Manufacturer: Origin Biomed Inc.
Category: homeopathic | Type: HUMAN OTC DRUG LABEL
Date: 20140214

ACTIVE INGREDIENTS: ACONITUM NAPELLUS 12 [hp_C]/113 g; HYPERICUM PERFORATUM 12 [hp_C]/113 g; LYCOPODIUM CLAVATUM SPORE 12 [hp_C]/113 g; TOXICODENDRON PUBESCENS LEAF 12 [hp_C]/113 g; CLAVICEPS PURPUREA SCLEROTIUM 12 [hp_C]/113 g; PHOSPHORUS 12 [hp_C]/113 g
INACTIVE INGREDIENTS: WATER; LAVENDER OIL; EUCALYPTUS OIL; GERANIUM OIL, ALGERIAN TYPE; TEA TREE OIL; GERANIOL; PROPYLENE GLYCOL; SORBITAN MONOOLEATE; BENZOIC ACID; ALCOHOL; SODIUM BENZOATE; BERGAMOT OIL; POLOXAMER 407

Drug Facts

Active Ingredients

Aconitum napellus 12C, Hypericum perforatum 12C, Lycopodium clavatum 12C, Phosphorus 12C, Rhus toxicodendron 12C, Secale cornutum 12C

Purpose

Topical analgesic

Uses

For rapid, temporary relief from pain described as shooting, burning, tingling and stabbing pain, especially in the hands and feet.

Warnings

- For external use only
- Avoid eye/mouth contact
- Strong floral aroma
- Do not use on broken skin
- Discontinue use if skin irritation develops

If condition worsens or if symptoms persist for more than 2 weeks consult your doctor.

Do not use if pregnant or breastfeeding.

Keep out of reach of children. If swallowed, get medical help or contact a Poison Control Center immediately.

Directions

Apply cream to the affected area up to 4 times daily.

Other information

Store at room temperature 59-86 degrees F (15-30 degrees C). Do not use if tamper seal is broken.

Inactive ingredients

water, bergamot oil, eucalyptus oil, geranium oil, geraniol, lavender oil, tea tree oil, geraniol, propylene glycol, poloxamer 407, sodium benzoate, benzoic-acid, and ethyl alcohol

Questions?

Call 1-902-423-5745
www.neuragen.com

PACKAGE LABEL

Pain Relief Cream
Fast acting relief from

- Shooting Pain
- Burning Pain
- Tingling Pain
- Stabbing Pain